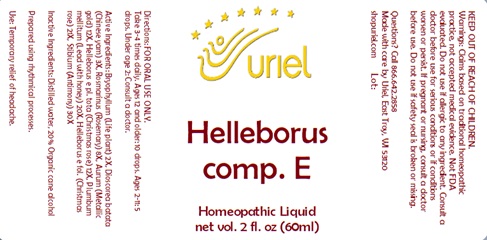 DRUG LABEL: Helleborus comp. E
NDC: 48951-5120 | Form: LIQUID
Manufacturer: Uriel Pharmacy Inc.
Category: homeopathic | Type: HUMAN OTC DRUG LABEL
Date: 20241217

ACTIVE INGREDIENTS: KALANCHOE DAIGREMONTIANA LEAF 2 [hp_X]/1 mL; ROSMARINUS OFFICINALIS FLOWERING TOP 8 [hp_X]/1 mL; ANTIMONY 30 [hp_X]/1 mL; GOLD 12 [hp_X]/1 mL; HELLEBORUS FOETIDUS ROOT 12 [hp_X]/1 mL; CHINESE YAM 3 [hp_X]/1 mL; HELLEBORUS NIGER ROOT 21 [hp_X]/1 mL; LEAD 20 [hp_X]/1 mL
INACTIVE INGREDIENTS: WATER; ALCOHOL

Helleborus comp. E

INDICATIONS AND USAGE

Directions: FOR ORAL USE ONLY.

DOSAGE AND ADMINISTRATION

Take 3-4 times daily. Ages 12 and older: 10 drops. Ages 2-11: 5 drops. Under age 2: Consult a doctor.

ACTIVE INGREDIENT

Active Ingredients: Bryophyllum (Life plant) 2X, Dioscorea batata (Chinese yam) 3X, Rosmarinus (Rosemary) 8X, Aurum (Metallic gold) 12X, Helleborus e pl. tota (Christmas rose) 12X, Plumbum mellitum (Lead with honey) 20X, Helleborus e fol. (Christmas rose) 21X, Stibium (Antimony) 30X

Inactive Ingredients: Distilled water, 20% Organic cane alcohol

Prepared using rhythmical processes.

PURPOSE

Use: Temporary relief of headache.

KEEP OUT OF REACH OF CHILDREN.

WARNINGS

Warnings: Claims based on traditional homeopathic practice, not accepted medical evidence. Not FDA evaluated. Do not use if allergic to any ingredient. Consult a doctor before use for serious conditions or if conditions worsen or persist. If pregnant or nursing, consult a doctor before use. Do not use if safety seal is broken or missing.

Questions? Call 866.642.2858
Made with care by Uriel, East Troy, WI 53120
shopuriel.com